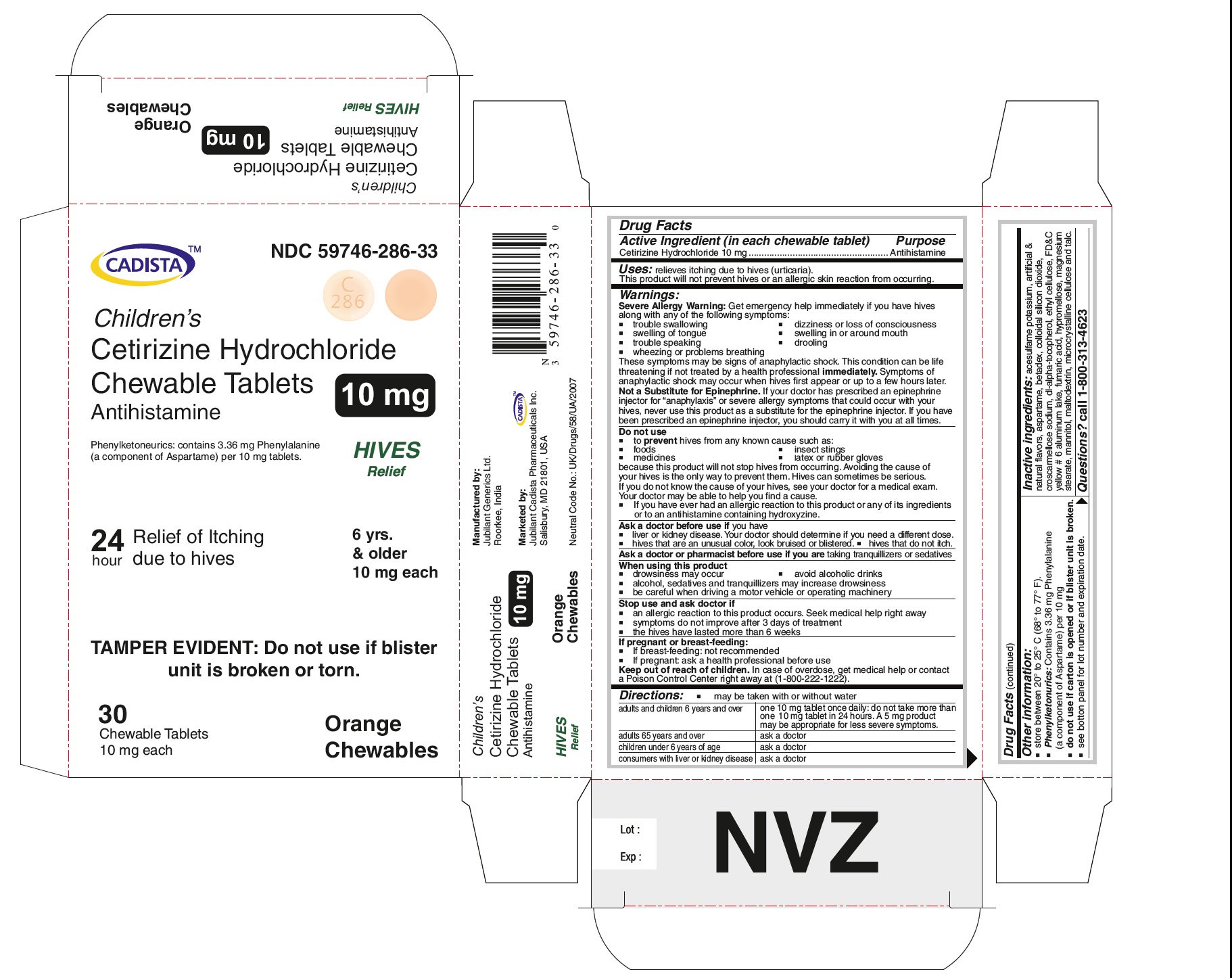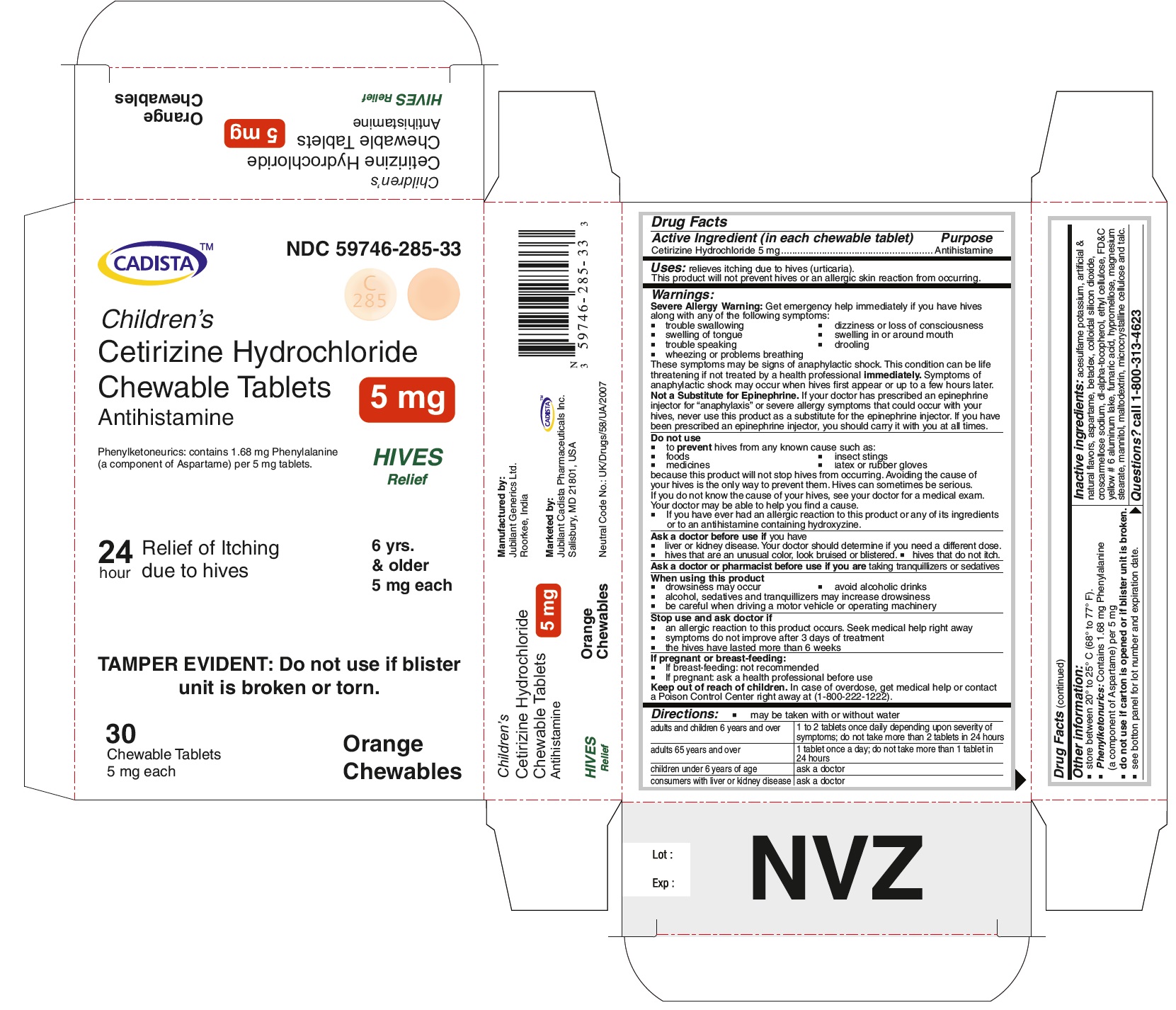 DRUG LABEL: cetirizine hydrochloride 
NDC: 59746-285 | Form: TABLET, CHEWABLE
Manufacturer: Jubilant Cadista Pharmaceuticals Inc.
Category: otc | Type: HUMAN OTC DRUG LABEL
Date: 20191230

ACTIVE INGREDIENTS: Cetirizine Hydrochloride 5 mg/1 1
INACTIVE INGREDIENTS: Acesulfame Potassium; Aspartame; Betadex; Silicon Dioxide; Croscarmellose Sodium; .alpha.-tocopherol, Dl-; Ethylcelluloses; Fd&c Yellow No. 6; Fumaric Acid; Hypromelloses; Magnesium Stearate; Mannitol; Maltodextrin; Cellulose, Microcrystalline; Talc

Children's
Cetirizine Hydrochloride Chewable Tablets
Antihistamine
Drug Facts

Active Ingredient (in each chewable tablet)

Cetirizine Hydrochloride 5 mg
Cetirizine Hydrochloride 10 mg

Purpose

Antihistamine

Uses:

relieves itching due to hives (urticaria).

This product will not prevent hives or an allergic skin reaction from occurring.

Warnings:

Severe Allergy Warning: Get emergency help immediately if you have hives along with any of the following symptoms:

- trouble swallowing
- swelling of tongue
- trouble speaking
- wheezing or problems breathing
- dizziness or loss of conciousness
- swelling in or around mouth
- drooling

These symptoms may be signs of anaphylactic shock. This condition can be life threatening if not treated by health professional immediately. Symptoms of anaphylactic shock may occur when hives first appear or up to a few hours later.

Not a Substitute for Epinephrine. If your doctor has prescribed an epinephrine injector for "anaphylaxis" or severe allergy symptoms that could occur with your hives, never use this product as a substitute for the epinephrine injector. If you have been prescribed an epinephrine injector, you should carry it with you at all times.

Do not use

- to prevent hives from any known cause such as:
- foods
- insect stings
- medicines
- latex or rubber gloves

because this product will not stop hives from occuring. Avoiding the cause of your hives is the only way to prevent them. Hives can sometimes be serious.
If you do not know the cause of your hives, see your doctor for a medical exam.
Your doctor may be able to help you find a cause.

● if you have ever had an allergic reaction to this product or any of its ingredients or to an antihistamine containing hydroxyzine.

Ask a doctor before use if you have

- liver or kidney disease. Your doctor should determine if you need a different dose.
- hives that are an unusual color, look bruised or blistered.
- hives that do not itch.

Ask a doctor or pharmacist before use if you are taking transquillizers or sedatives

When using this product

- drowsiness may occur
- avoid alcoholic drinks
- alcohol, sedatives and tranquilizers may increase drowsiness
- be careful when driving a motor vehicle or operating machinery

Stop use and ask doctor if

- an allergic reaction to this product occurs. Seek medical help right away
- symptoms do not improve after 3 days of treatment
- the hives have lasted more than 6 weeks

If pregnant or breast-feeding:

- if breast-feeding: not recommended
- if pregnant: ask a health professional before use

Directions:

● may be taken with and without water

For Cetirizine Hydrochloride Chewable Tablets 5 mg

adults and children 6 years and over | 1 to 2 tablets once daily depending upon severity of symptoms; do not take more than 2 tablets in 24 hours
adults 65 years and over | 1 tablet once a day; do not take more than 1 tablet in 24 hours
children under 6 years of age | ask a doctor
consumers with liver or kidney disease | ask a doctor

Cetirizine Hydrochloride Chewable Tablets 10 mg

adults and children 6 years and over | one 10 mg tablet once daily; do not take more than one 10 mg tablet in 24 hours. A 5 mg product may be appropriate for less severe symptoms.
adults 65 years and over | ask a doctor
children under 6 years of age | ask a doctor
consumers with liver or kidney disease | ask a doctor

Other information:

- store between 20º to 25º C (68º to 77º F).
- Phenylketonurics: Contains 1.68 mg Phenylalanine (a component of Aspartame) per 5 mg
- Phenylketonurics: Contains 3.36 mg Phenylalanine (a component of Aspartame) per 10 mg
- do not use if carton is opened or if blister unit is broken.
- see bottom panel for lot number and expiration date.

Inactive ingredients:

acesulfame potassium, artificial & natural flavors,aspartame, betadex, colloidal silicon dioxide, croscarmellose sodium, dl-alpha-tocopherol, ethyl cellulose, FD&C yellow # 6 aluminum lake, fumaric acid, hypromellose, magnesium stearate, mannitol, maltodextrin, microcrystalline cellulose and talc.

Questions? call 1-800-313-4623

Manufactured by:
Jubilant Generics Ltd.
Roorkee-247661, India

Marketed by:
Jubilant Cadista Pharmaceuticals Inc.
Salisbury, MD 21801, USA

Revised : November / 2014

PACKAGE LABEL.PRINCIPAL DISPLAY PANEL

CADISTA NDC 59746-285-33
Children's
Cetirizine Hydrochloride Chewable Tablets 5 mg
Antihistamine
Phenylketonurics: contains 1.68 mg Phenyalanine (a component of Aspartame) per 5 mg tablets.
HIVES Relief
24 hour Relief of Itching due to hives
6 yrs. & older 5 mg each
TAMPER EVIDENT : Do not use if blister unit is broken or torn.
30 Chewable Tablets Orange Chewables
5 mg each

Cetirizine Hydrochloride Chewable Tablets 5 mg Hives Relief

CADISTA NDC 59746-286-33
Children's
Cetirizine Hydrochloride Chewable Tablets 10 mg
Antihistamine
Phenylketonurics: contains 3.36 mg phenyalanine (a component of Aspartame) per 10 mg tablets.
HIVES Relief
24 hour Relief of Itching due to hives
6 yrs. & older 10 mg each
TAMPER EVIDENT : Do not use if blister unit is broken or torn.
30 Chewable Tablets Orange Chewables
10 mg each

Cetirizine Hydrochloride Chewable Tablets 10 mg Hives Relief